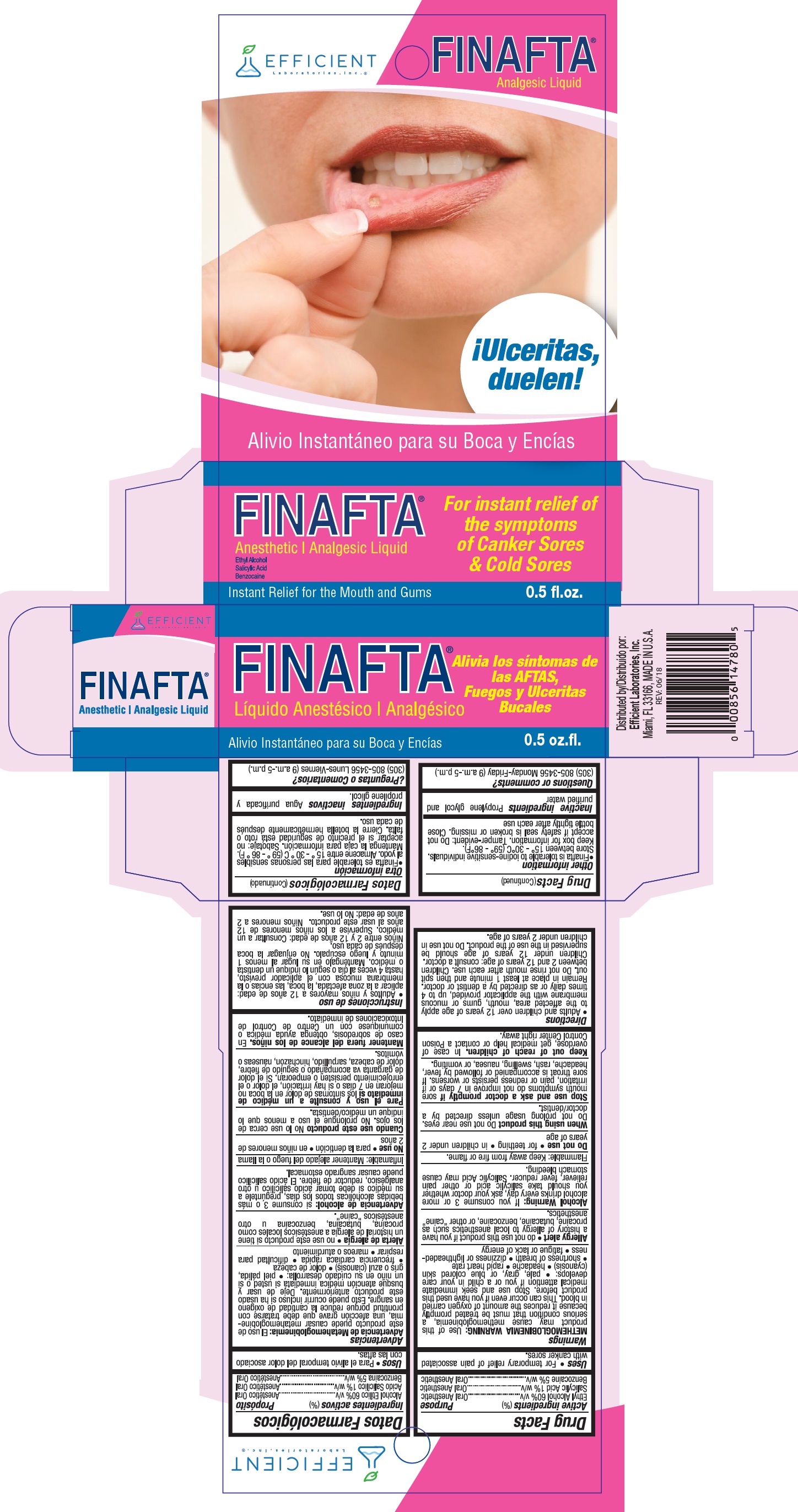 DRUG LABEL: Finafta
NDC: 58593-780 | Form: LIQUID
Manufacturer: Efficient Laboratories Inc.
Category: otc | Type: HUMAN OTC DRUG LABEL
Date: 20230807

ACTIVE INGREDIENTS: ALCOHOL 60 mL/100 mL; SALICYLIC ACID 1 mg/100 mL; BENZOCAINE 5 mg/100 mL
INACTIVE INGREDIENTS: PROPYLENE GLYCOL; WATER

Finafta

Active Ingredients: (%) Purpose

Ethyl Alcohol 60% v/v........................Anesthetic/Analgesic

Salicylic Acid 1% w/v.........................Anesthetic/Analgesic

Benzocaine USP 5% w/v...................Anesthetic/Analgesic

Purpose

Anesthetic/Analgesic

Uses

For temporary relief of pain associated with canker sores

Warnings

Methemoglobinemia warning: Use of this product may cause mthemoglobinemia, a serious condition that must be treated promptyly because it reduces the amount of oxygen carried in the blood. This can occur even if you have used this product before. Stop use and seek immediate medical attention if you or a child in your care develops:

- pale, gray, or blue colored skin (cyanosis)
- headache
- rapid heart rate
- shortness of breath
- dizziness or lightheadedness
- fatigue or lack of enegry

Allegry alert

- do not use this product if you have a history of allergy to local anesthetics such as prcaine, butacaine, bezocaine, or other "caine" anesthetics.

Alcogol Warning: If you consume 3 or more alcoholic drinks every day, ask your doctor whehter you should take slicylic acid or other pain reliever, fever reducer. Salicylic acid may cause stomach bleeding.

Flammable: Keep away from fire or flame.

Do not use

- for teething
- in children under 2 years of age

When using this prduct Do not use near eyes. Do not prolong usage unless directed by a doctor/dentist.

Stop use and ask a doctor promptly if sore mouth symptoms do not improve in 7 days or if irritation, pain or redness persists or worsens. If you sore throat is accompanied or followed by fever, headache, rash, swelling, nausea, or vomiting.

Keep out of reach of children. In case of accidental overdose: Get medical help or contact a Poison Control Center right away.

Directions

Adults and children over 12 years of age apply to the affected area, mouth, gums or mucous membrane with the applicator provided, up to 4 times daily or as directed by a dentist or doctor. Remain in place at least 1 minute and then spit out. Do not rinse mouth after each use. Children under 12 years of age should be supervised in the use of the product. Do not use in children under 2 years of age.

Questions or comments?

305-805-3456

Monday-Friday (9 a.m. - 5 p.m. EST)

www.efficientlabs.com

Inactive Ingredients:

Propylene Glycol and Purified Water.